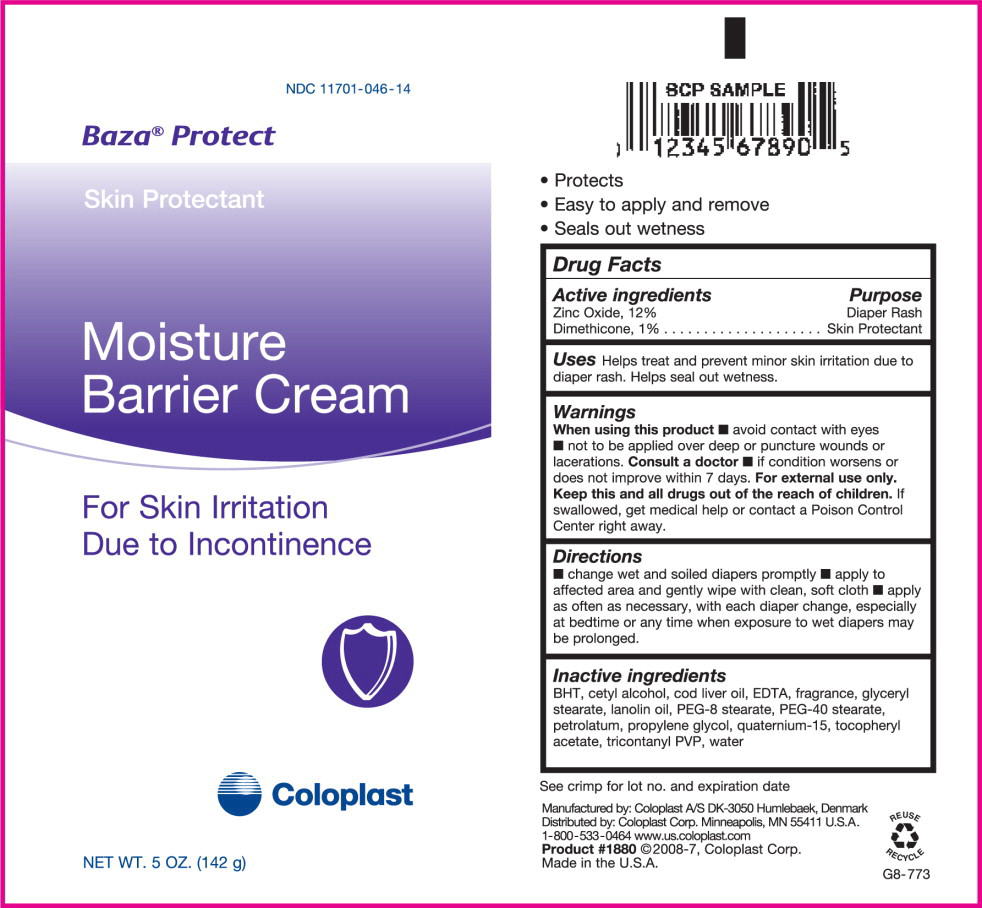 DRUG LABEL: Baza Protect
NDC: 11701-046 | Form: CREAM
Manufacturer: Coloplast Manufacturing US, LLC
Category: otc | Type: HUMAN OTC DRUG LABEL
Date: 20241226

ACTIVE INGREDIENTS: ZINC OXIDE 120 mg/1 g; DIMETHICONE 10 mg/1 g
INACTIVE INGREDIENTS: CETYL ALCOHOL; GLYCERYL MONOSTEARATE; TRICONTANYL POVIDONE; PETROLATUM; LANOLIN; PEG-8 STEARATE; PROPYLENE GLYCOL; PEG-40 STEARATE; EDETIC ACID; COD LIVER OIL; .ALPHA.-TOCOPHEROL ACETATE, D-; BUTYLATED HYDROXYTOLUENE; QUATERNIUM-15; WATER

Baza® Protect
Skin Protectant
Moisture Barrier Cream

For Skin Irritation Due to Incontinence

- Protects
- Easy to apply and remove
- Seals out wetness

Drug Facts

Active ingredients

Zinc Oxide, 12%

Dimethicone, 1 %

Purpose

Diaper Rash

Skin Protectant

INDICATIONS AND USAGE

Uses Helps treat and prevent minor skin irritation due to

diaper rash. Helps seal out wetness.

Warnings

When using this product

- avoid contact with eyes
- not to be applied over deep or puncture wounds or lacerations.

Consult a doctor

- if condition worsens or does not improve within 7 days.

For external use only.

KEEP OUT OF REACH OF CHILDREN

Keep this and all drugs out of the reach of children. If swallowed, get medical help or contact a Poison Control

Center right away.

Directions

- change wet and soiled diapers promptly
- apply to affected area and gently wipe with clean, soft cloth
- apply as often as necessary, with each diaper change, especially at bedtime or any time when exposure to wet diapers may be prolonged.

Inactive ingredients

BHT, cetyl alcohol, cod liver oil, EDTA, fragrance, glyceryl stearate, lanolin oil, PEG-8 stearate, PEG-40 stearate, petrolatum, propylene glycol, quaternium-15, tocopheryl acetate, tricontanyl PVP, water

See crimp for lot no. and expiration date

Manufactured by: Coloplast A/S DK-3050 Humlebaek, Denmark
Distributed by: Coloplast Corp. Minneapolis, MN 55411 U.S.A.
1-800-533-0464 www.us.cobplast.com
Product #1880 ©2008-7, Coloplast Corp.
Made in the U.S.A.

G8-773

PACKAGE LABEL

PRINCIPAL DISPLAY PANEL - NET WT. 5 OZ. (142g)

NDC 11701-046-14

Baza® Protect

Skin Protectant

Moisture Barrier Cream

For Skin Irritation Due to Incontinence

Coloplast

NET WT. 5 OZ. (142 g)